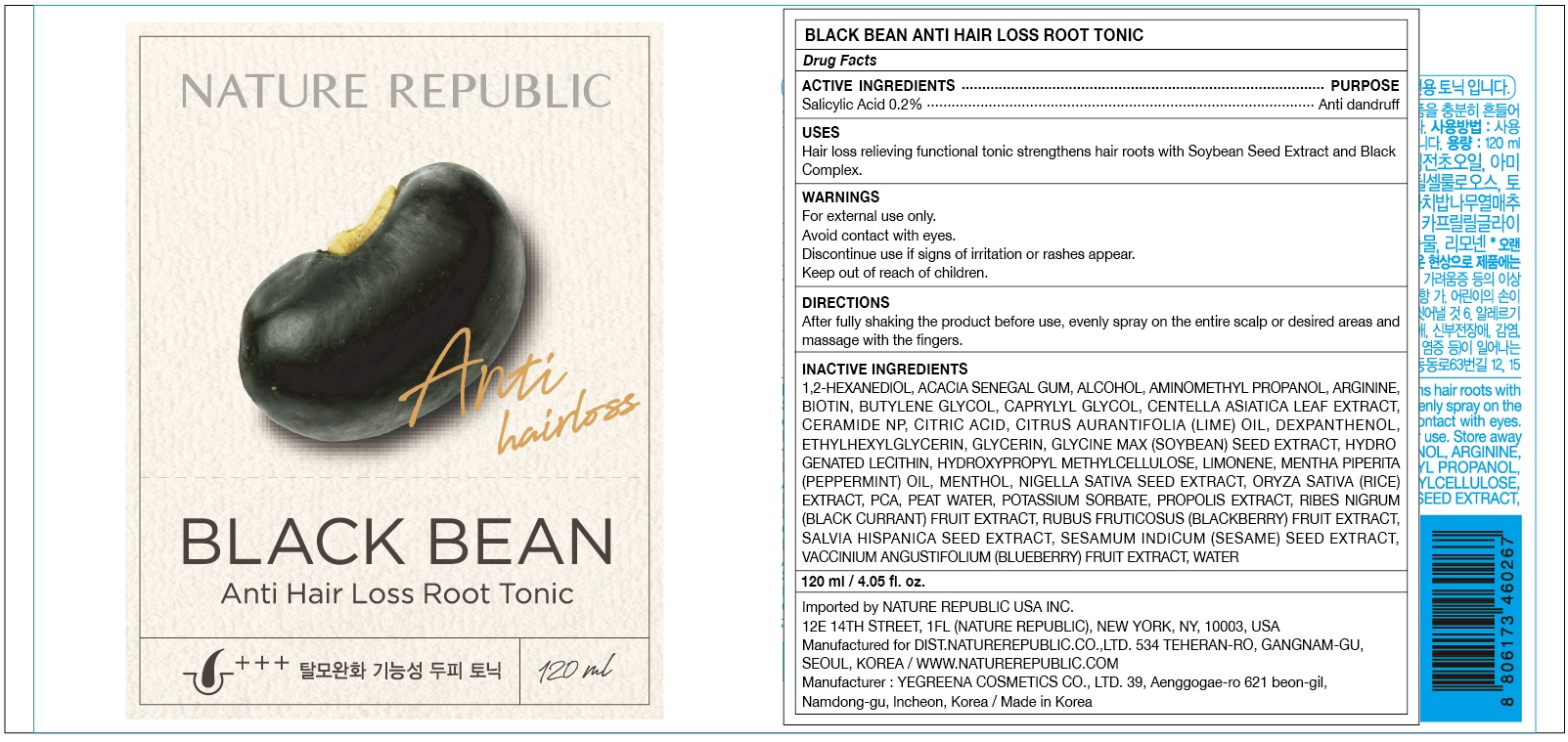 DRUG LABEL: BLACK BEAN ANTI HAIR LOSS ROOT TONIC
NDC: 51346-534 | Form: SPRAY
Manufacturer: NATURE REPUBLIC CO., LTD.
Category: otc | Type: HUMAN OTC DRUG LABEL
Date: 20201029

ACTIVE INGREDIENTS: Salicylic Acid 0.24 g/120 mL
INACTIVE INGREDIENTS: 1,2-Hexanediol; ACACIA

ACTIVE INGREDIENT

Salicylic Acid 0.2%

INACTIVE INGREDIENTS

1,2-Hexanediol, Acacia Senegal Gum, Alcohol, Aminomethyl Propanol, Arginine, Biotin, Butylene Glycol, Caprylyl Glycol, Centella Asiatica Leaf Extract, Ceramide NP, Citric Acid, Citrus Aurantifolia (Lime) Oil, Dexpanthenol, Ethylhexylglycerin, Glycerin, Glycine Max (Soybean) Seed Extract, Hydrogenated Lecithin, Hydroxypropyl Methylcellulose, Limonene, Mentha Piperita (Peppermint) Oil, Menthol, Nigella Sativa Seed Extract, Oryza Sativa (Rice) Extract, PCA, Peat water, Potassium Sorbate, Propolis Extract, Ribes Nigrum (Black Currant) Fruit Extract, Rubus Fruticosus (Blackberry) Fruit Extract, Salvia Hispanica Seed Extract, Sesamum Indicum (Sesame) Seed Extract, Vaccinium Angustifolium (Blueberry) Fruit Extract, Water

PURPOSE

Anti dandruff

WARNINGS

For external use only.
Avoid contact with eyes.
Discontinue use if signs of irritation or rashes appear.
Keep out of reach of children.

KEEP OUT OF REACH OF CHILDREN

Uses

Hair loss relieving functional tonic strengthens hair roots with Soybean Seed Extract and Black Complex.

Directions

After fully shaking the product before use, evenly spray on the entire scalp or desired areas and massage with the fingers.